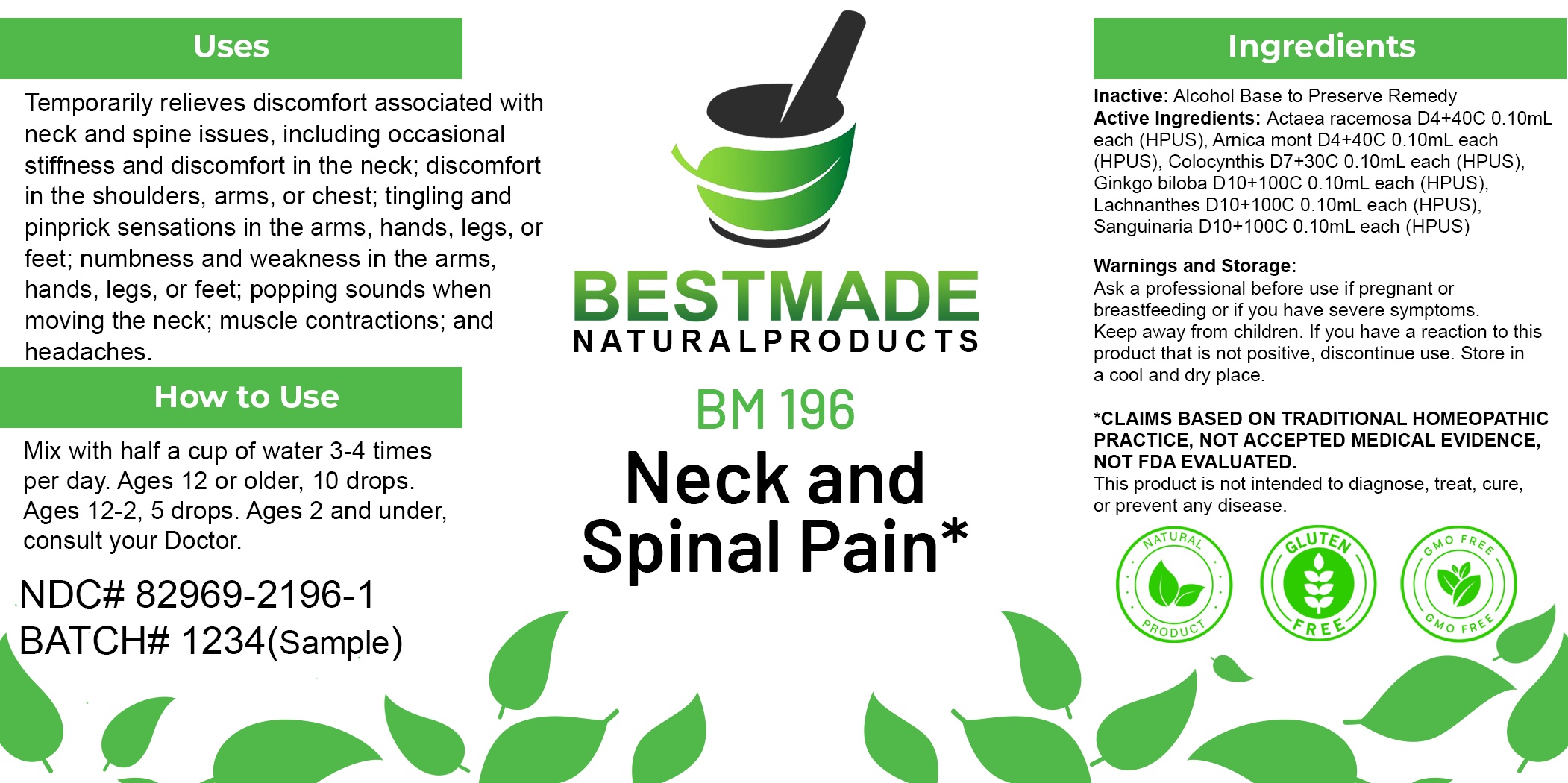 DRUG LABEL: Bestmade Natural Products BM196
NDC: 82969-2196 | Form: LIQUID
Manufacturer: Bestmade Natural Products
Category: homeopathic | Type: HUMAN OTC DRUG LABEL
Date: 20250225

ACTIVE INGREDIENTS: LACHNANTHES CAROLINIANA WHOLE 30 [hp_C]/30 [hp_C]; SANGUINARIA CANADENSIS ROOT 30 [hp_C]/30 [hp_C]; GINKGO 30 [hp_C]/30 [hp_C]; BLACK COHOSH 30 [hp_C]/30 [hp_C]; CITRULLUS COLOCYNTHIS FRUIT PULP 30 [hp_C]/30 [hp_C]; ARNICA MONTANA WHOLE 30 [hp_C]/30 [hp_C]
INACTIVE INGREDIENTS: ALCOHOL 30 [hp_C]/30 [hp_C]

BM196

DOSAGE AND ADMINISTRATION

How to Use

Mix with half a cup of water 3-4 times per day. Ages 12 or older, 10 drops. Ages 12-2, 5 drops. Ages 2 and under, consult your Doctor.

Inactive:

Alcohol Base to Preserve Product

ACTIVE INGREDIENTS

Actaea racemosa D4+40C 0.10mL each (HPUS), Arnica mont D4+40C 0.10mL each (HPUS), Colocynthis D7+30C 0.10mL each (HPUS), Ginkgo biloba D10+100C 0.10mL each (HPUS), Lachnanthes D10+100C 0.10mL each (HPUS), Sanguinaria D10+100C 0.10mL each (HPUS)

KEEP OUT OF REACH OF CHILDREN

Warnings and Storage:

Ask a professional before use if pregnant or breastfeeding or if you have severe symptoms.

Keep away from children. If you have a reaction to this product that is not positive, discontinue use. Store in a cool and dry place

*CLAIMS BASED ON TRADITIONAL HOMEOPATHIC PRACTICE, NOT ACCEPTED MEDICAL EVIDENCE NOT FDA EVALUATED.
This product is not intended to diagnose, treat, cure, or prevent any disease.

Warnings and Storage:

Ask a professional before use if pregnant or breastfeeding or if you have severe symptoms.

Keep away from children. If you have a reaction to this product that is not positive, discontinue use. Store in a cool and dry place

*CLAIMS BASED ON TRADITIONAL HOMEOPATHIC PRACTICE, NOT ACCEPTED MEDICAL EVIDENCE NOT FDA EVALUATED.
This product is not intended to diagnose, treat, cure, or prevent any disease.

Uses
Temporarily relieves discomfort associated with neck and spine issues, including occasional stiffness and discomfort in the neck; discomfort in the shoulders, arms, or chest; tingling and pinprick sensations in the arms, hands, legs, or feet; numbness and weakness in the arms, hands, legs, or feet; popping sounds when moving the neck; muscle contractions: and headaches.

Uses
Temporarily relieves discomfort associated with neck and spine issues, including occasional stiffness and discomfort in the neck; discomfort in the shoulders, arms, or chest; tingling and pinprick sensations in the arms, hands, legs, or feet; numbness and weakness in the arms, hands, legs, or feet; popping sounds when moving the neck; muscle contractions: and headaches.

Entire package label